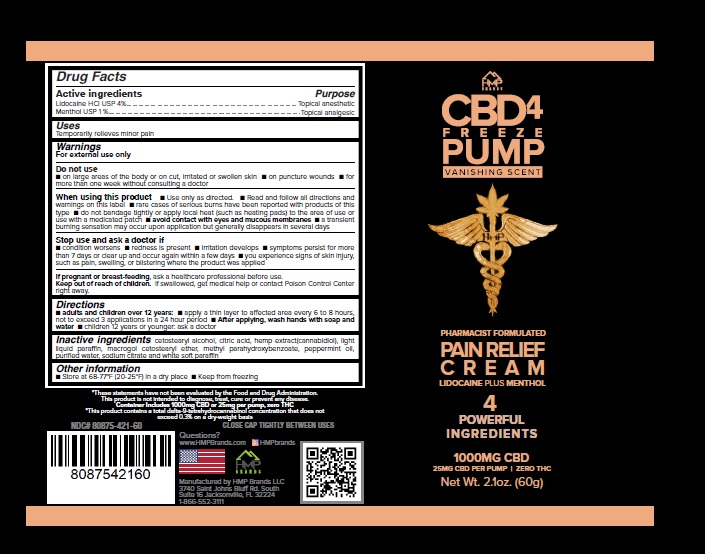 DRUG LABEL: CBD4 FREEZE PUMP VANISHING SCENT
NDC: 80875-421 | Form: CREAM
Manufacturer: HMP BRANDS, LLC
Category: otc | Type: HUMAN OTC DRUG LABEL
Date: 20201022

ACTIVE INGREDIENTS: LIDOCAINE 4 g/100 g; MENTHOL 1 g/100 g
INACTIVE INGREDIENTS: CETOSTEARYL ALCOHOL; CITRIC ACID MONOHYDRATE; CANNABIDIOL; LIGHT MINERAL OIL; POLYOXYL 20 CETOSTEARYL ETHER; METHYLPARABEN; PEPPERMINT OIL; WATER; SODIUM CITRATE; PETROLATUM

Active Ingredient Purpose

Lidocaine HCI USP 4%.............................. Topical anesthetic

Menthol USP 1 % .................................... Topical analgesic

Use

Temporarily relieves minor pain.

Warnings

For external use only.

Do not use

- on large areas of the body or on cut, irritated or swollen skin.
- on puncture wounds.
- for more than one week without consulting a doctor.

When using this product

- Use only as directed.
- Read and follow all directions and warnings on this label.
- Rare cases of serious burns have been reported with products of this type.
- Do not bandage tightly or apply local heat (such as heating pads) to the area of use or use with a medicated patch.
- Avoid contact with eyes and mucous membranes.
- A transient burning sensation may occur upon application but generally disappears in several days.

Stop use and ask a doctor if

- condition worsens.
- redness is present.
- irritation develops.
- symptoms persist for more than 7 days or clear up and occur again within a few days.
- You experience signs of skin injury, such as pain, swelling, or blistering where the product was applied.

If pregnant or breast-feeding, ask a healthcare professional before use..

Keep out of reach of children. If swallowed, get medical help or contact a Poison Control Center right away.

Directions

adults and children over 12 years:

- Apply a thin layer to affected area every 6 to 8 hours, not to exceed 3 applications in a 24 hour period.
- After applying, wash hands with soap and water

Children 12 years or younger: ask a doctor

Other information

- Store at 68-77°F (20-25°F) in a dry place
- Keep from freezing

Inactive ingredients

cetostearyl alcohol, citric acid, hemp extract(cannabidiol), light liquid paraffin, macrogol cetostearyl ether, methyl parahydroxybenzoate, peppermint oil, purified water, sodium citrate and white soft paraffin.